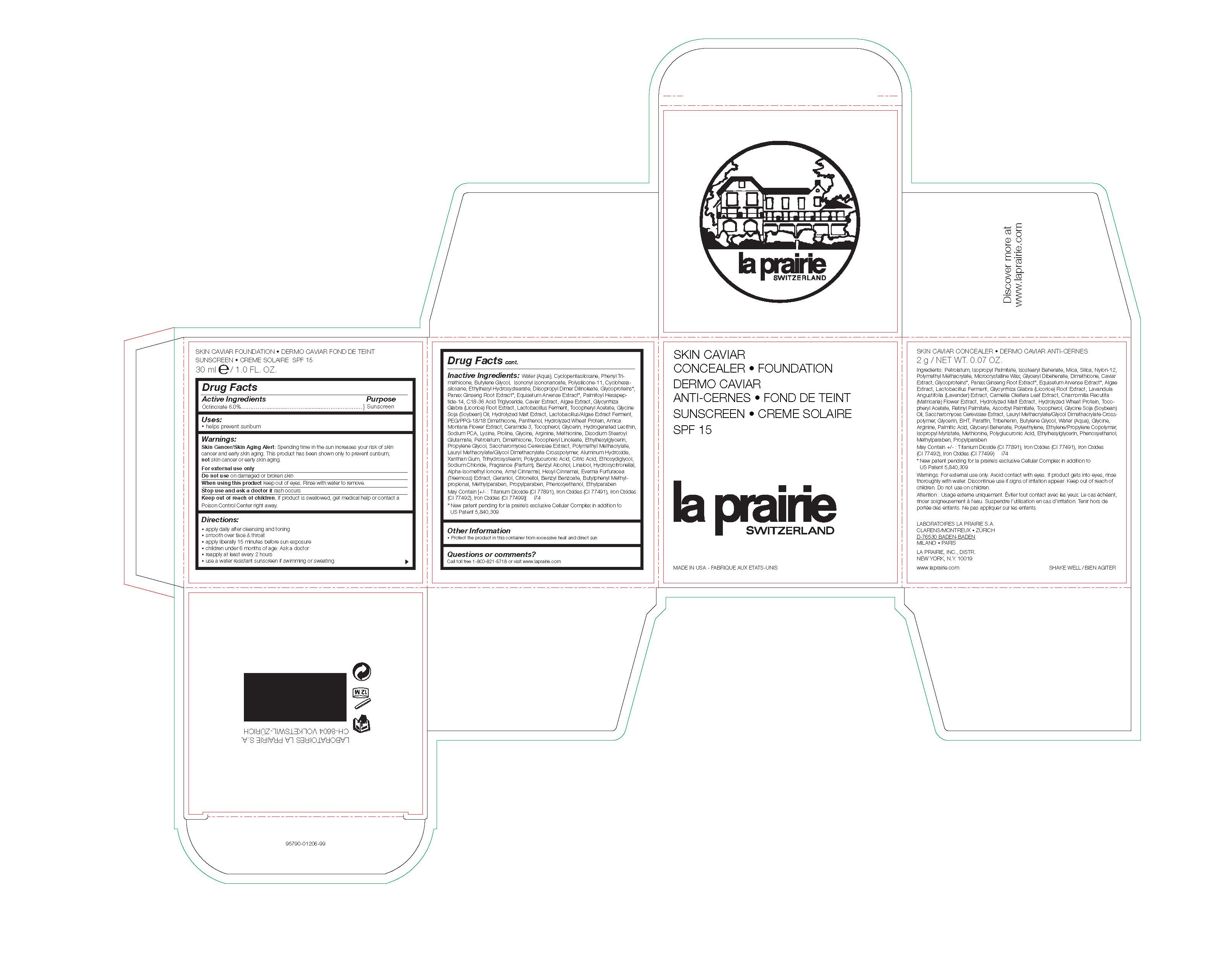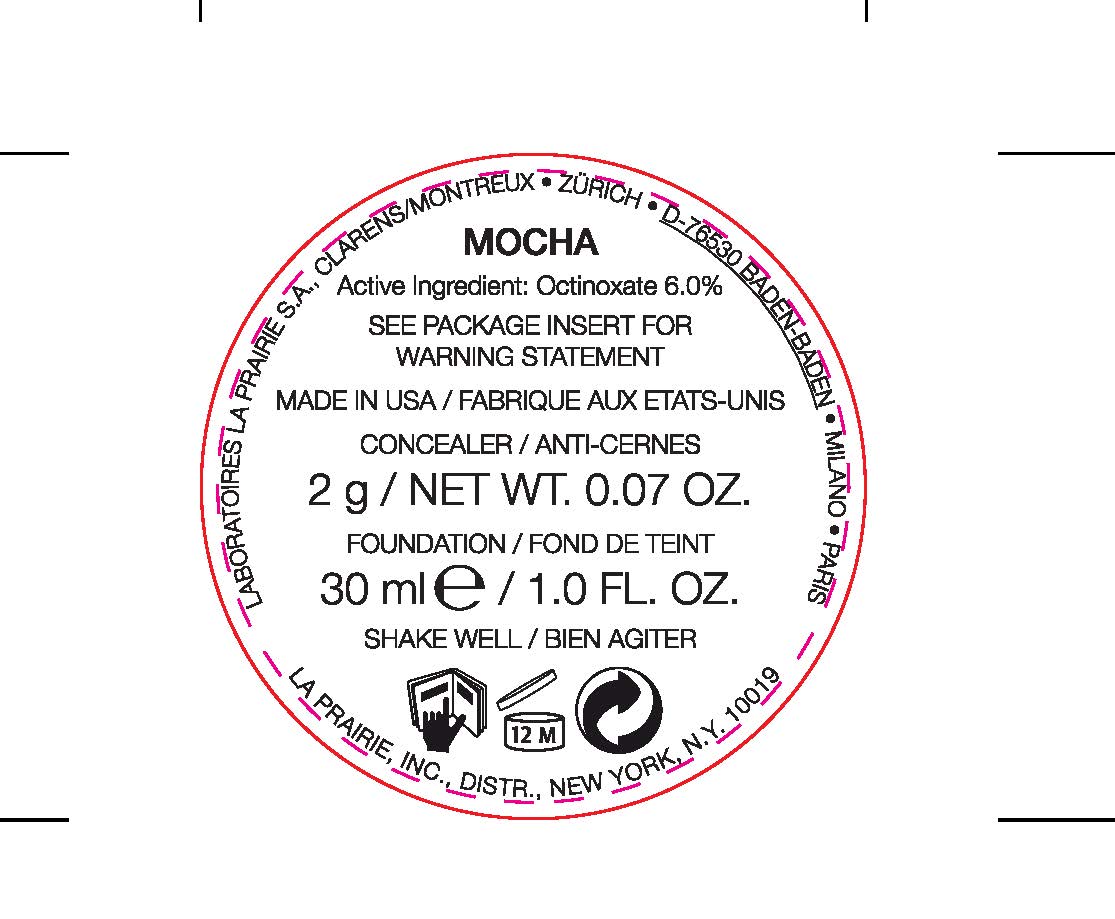 DRUG LABEL: Skin Caviar Foundation Sunscreen SPF 15 - Mocha
NDC: 68026-120 | Form: LOTION
Manufacturer: La Prairie, Inc
Category: otc | Type: HUMAN OTC DRUG LABEL
Date: 20181120

ACTIVE INGREDIENTS: OCTINOXATE 60 mg/1 mL
INACTIVE INGREDIENTS: ETHYLPARABEN; BENZYL ALCOHOL; PANTHENOL; .ALPHA.-TOCOPHEROL LINOLEATE, D-; POLY(METHYL METHACRYLATE; 450000 MW); CERAMIDE 3; WATER; CYCLOMETHICONE 5; PHENYL TRIMETHICONE; BUTYLENE GLYCOL; ETHYLHEXYL HYDROXYSTEARATE; TRIHYDROXYSTEARIN; C18-36 ACID TRIGLYCERIDE; SODIUM CHLORIDE; DISODIUM STEAROYL GLUTAMATE; FERRIC OXIDE RED; PHENOXYETHANOL; ALUMINUM HYDROXIDE; METHYLPARABEN; ISONONYL ISONONANOATE; DIMETHICONE/VINYL DIMETHICONE CROSSPOLYMER (SOFT PARTICLE); CYCLOMETHICONE 6; PROPYLPARABEN; DIETHYLENE GLYCOL MONOETHYL ETHER; LAURYL METHACRYLATE/GLYCOL DIMETHACRYLATE CROSSPOLYMER; DIISOPROPYL DILINOLEATE; CITRONELLAL; ISOMETHYL-.ALPHA.-IONONE; PROPYLENE GLYCOL; PSEUDEVERNIA FURFURACEA; BENZYL BENZOATE; GERANIOL; ARNICA MONTANA FLOWER; BUTYLPHENYL METHYLPROPIONAL; LACTOBACILLUS REUTERI; SODIUM PYRROLIDONE CARBOXYLATE; HYDROGENATED SOYBEAN LECITHIN; HYDROLYZED WHEAT PROTEIN (ENZYMATIC, 3000 MW); GLYCINE; CAVIAR, UNSPECIFIED; XANTHAN GUM; GLYCYRRHIZA GLABRA; SACCHAROMYCES CEREVISIAE; ASIAN GINSENG; LYSINE; ARGININE; ETHYLHEXYLGLYCERIN; EQUISETUM ARVENSE BRANCH; METHIONINE; GLUCURONIC ACID; PROLINE; CITRIC ACID MONOHYDRATE; TITANIUM DIOXIDE; FERRIC OXIDE YELLOW; FERROSOFERRIC OXIDE; ALPHA-TOCOPHEROL ACETATE; GLYCERIN; DIMETHICONE; LACTOBACILLUS RHAMNOSUS; TOCOPHEROL; HYDROXYCITRONELLAL; .ALPHA.-AMYLCINNAMALDEHYDE; .ALPHA.-HEXYLCINNAMALDEHYDE; PETROLATUM; SARGASSUM FILIPENDULA; PEG/PPG-18/18 DIMETHICONE; SOYBEAN OIL; LINALOOL, (+/-)-

Active Ingredients

Octinoxate 6.0%

Purpose

Sunscreen

Uses

Helps Prevent Sunburn

Warnings

Skin Cancer/Skin Aging Alert: Spending time in the sun increase your risk of skin cancer and early skin aging. This product has been shown only to prevent sunburn, not skin cancer or early skin aging.

For external use only

Do not use

on damaged or broken skin

When using this product

Keep out of eyes. Rinse with water to remove.

Stop use and ask a doctor if

rash occurs

Keep out of reach of children

If product is swallowed, get medical help or contact a Poison Control Center right away.

Directions

Apply Daily After Cleansing and Toning

Smooth over face and throat

Apply liberally 15 minutes before sun exposure

Children under 6 months of age: Ask a doctor

Reapply at least every 2 hours

Use a water resistance sunscreen if swimming or sweating

Inactive Ingredients

Water (Aqua), Cyclopentasiloxane, Phenyl Trimethicone,
Butylene Glycol, Isononyl Isononanoate, Polysilicone-11, Cyclohexasiloxane,
Ethylhexyl Hydroxystearate, Diisopropyl Dimer Dilinoleate, Glycoproteins*,
Panax Ginseng Root Extract*, Equisetum Arvense Extract*, Palmitoyl Hexapeptide-
14, C18-36 Acid Triglyceride, Caviar Extract, Algae Extract, Glycyrrhiza
Glabra (Licorice) Root Extract, Lactobacillus Ferment, Tocopheryl Acetate, Glycine
Soja (Soybean) Oil, Hydrolyzed Malt Extract, Lactobacillus/Algae Extract Ferment,
PEG/PPG-18/18 Dimethicone, Panthenol, Hydrolyzed Wheat Protein, Arnica
Montana Flower Extract, Ceramide 3, Tocopherol, Glycerin, Hydrogenated Lecithin,
Sodium PCA, Lysine, Proline, Glycine, Arginine, Methionine, Disodium Stearoyl
Glutamate, Petrolatum, Dimethicone, Tocopheryl Linoleate, Ethylhexylglycerin,
Propylene Glycol, Saccharomyces Cerevisiae Extract, Polymethyl Methacrylate,
Lauryl Methacrylate/Glycol Dimethacrylate Crosspolymer, Aluminum Hydroxide,
Xanthan Gum, Trihydroxystearin, Polyglucuronic Acid, Citric Acid, Ethoxydiglycol,
Sodium Chloride, Fragrance (Parfum), Benzyl Alcohol, Linalool, Hydroxycitronellal,
Alpha-Isomethyl Ionone, Amyl Cinnamal, Hexyl Cinnamal, Evernia Furfuracea
(Treemoss) Extract, Geraniol, Citronellol, Benzyl Benzoate, Butylphenyl Methylpropional,
Methylparaben, Propylparaben, Phenoxyethanol, Ethylparaben
May Contain [+/- : Titanium Dioxide (CI 77891), Iron Oxides (CI 77491), Iron Oxides
(CI 77492), Iron Oxides (CI 77499)] i74

Other information

Protect the product in this container from excessive heat and direct sun

Questions or Comments?

Call toll free 1-800-821-5718 or visit www.laprairie.com

Principle Display Panel

Mocha

Active Ingredient: Octinoxate 6.0% SEE PACKAGE INSERT FOR WARNING STATEMENT

30 ml e / 1.0 FL. OZ.

MADE IN USA - FABRIQUE AUX ETATS-UNIS

LABORATOIRES LA PRAIRIE S.A CLARENS/MONTREUX • ZURICH D-78530 BADEN-BADEN MILANO • PARIS

LA PRAIRIE, INC. DISTR. NEW YORK, N.Y. 10019

SHAKE WELL / BIEN AGITER

LABORATOIRES LA PRAIRIE S.A., CLARENS/MONTREUX • ZURICH • D-BADEN-BADEN • MILANO • PARIS

LA PRAIRIE, INC., DISTR., NEW YORK, N.Y. 10019

MADE IN USA / FABRIQUE AUX ETATS-UNIS

CONCEALER / ANTI-CERNES 2 g / NET WT. 0.07 OZ.

FOUNDATION / FOND DE TEINT 30 ml e / 1.0 FL. OZ.

SHAKE WELL / BIEN AGITER

SKIN CAVIAR CONCEALER . FOUNDATION SPF 15 la prairie SWITZERLAND 30ml e / 1.0 FL. OZ.